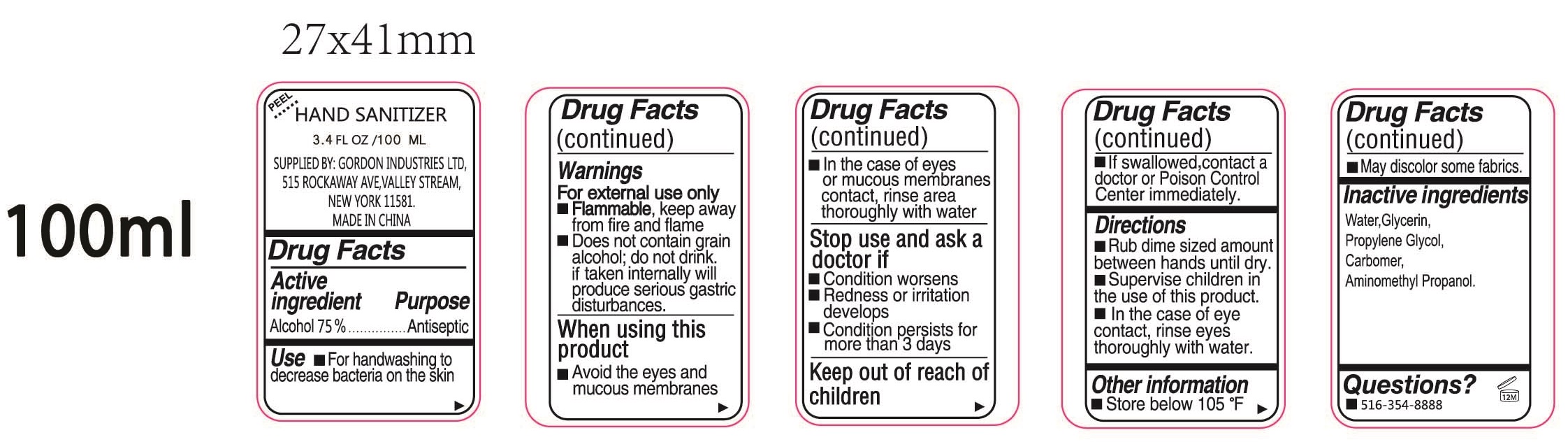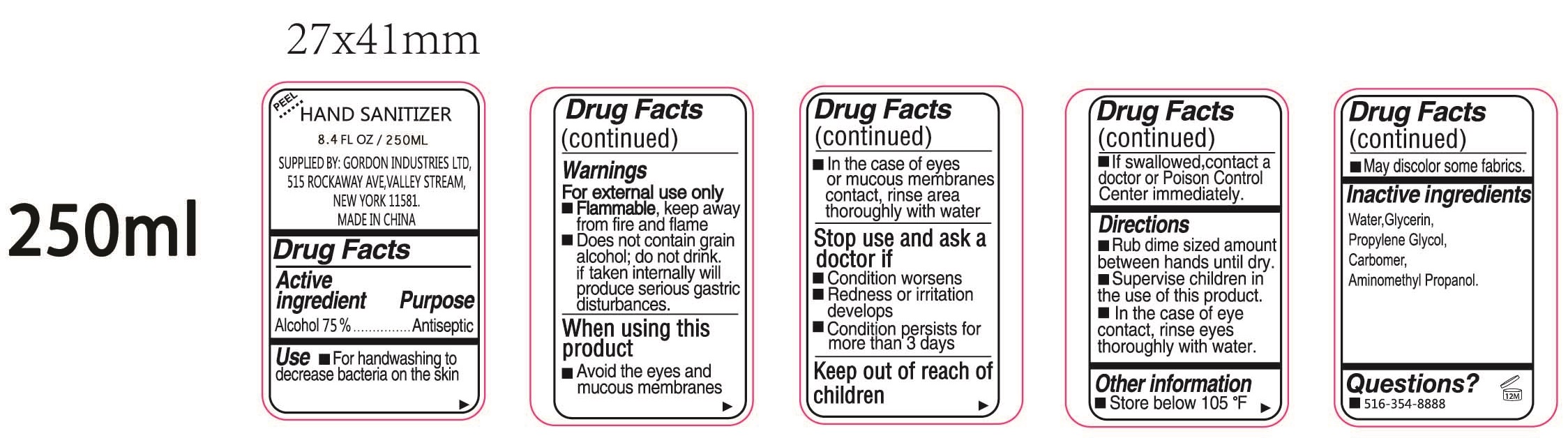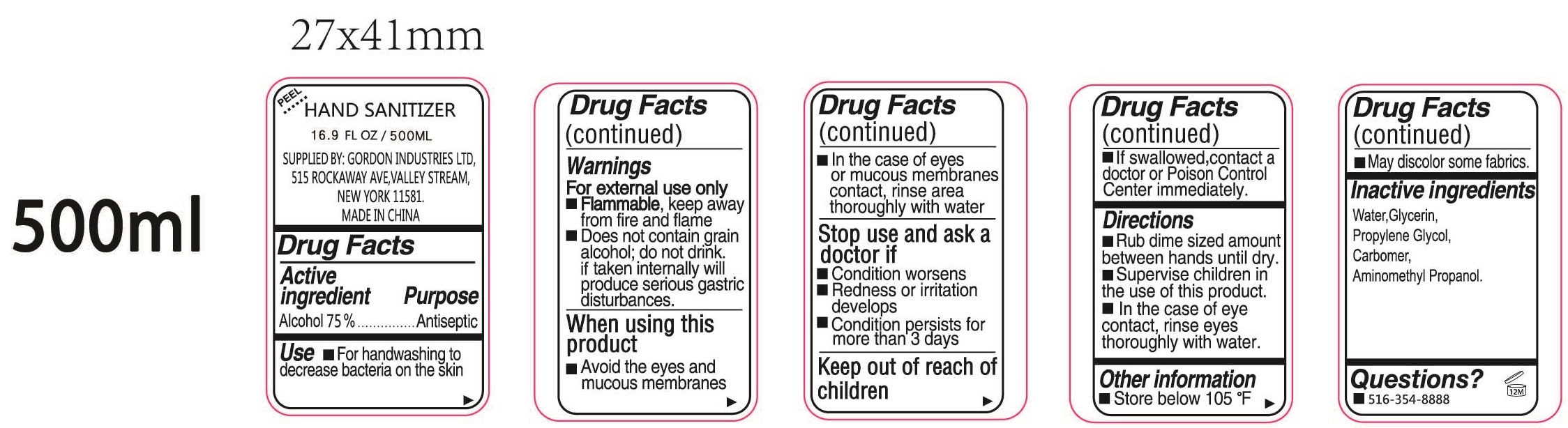 DRUG LABEL: Hand Sanitizer
NDC: 74979-002 | Form: LIQUID
Manufacturer: Robert Gordon Ind. Ltd.
Category: otc | Type: HUMAN OTC DRUG LABEL
Date: 20240209

ACTIVE INGREDIENTS: ALCOHOL 0.75 mL/1 mL
INACTIVE INGREDIENTS: WATER; GLYCERIN; PROPYLENE GLYCOL; CARBOMER HOMOPOLYMER, UNSPECIFIED TYPE; AMINOMETHYLPROPANOL

Hand Sanitizer

Active ingredient

Alcohol 75 %

Purpose

Antiseptic

Use

- For handwashing to decrease bacteria on the skin

Warnings

For external use only

- Flammable, keep away from fire and flame
- Does not contain grain alcohol; do not drink if taken internally will produce serious gastric distric disturbances.

When using this product

- Avoid the eyes and mucous membranes
- In the case of eyes or mucous membranes contact, rinse area thoroughly with water

Stop use and ask a doctor if

- Condition worsens
- Redness or irritation develops
- Condition persists for more than 3 days

Keep out of reach of children

- If swallowed,contact a doctor or Poison Control Center immediately.

Directions

- Rub dime sized amount between hands until dry.
- Supervise children in the use of this product.
- In the case of eye contact, rinse eyes thoroughly with water.

Other information

- Store below 105 °F
- May discolor some fabrics.

Inactive ingredients

Water,Glycerin, Propylene Glycol, Carbomer, Aminomethyl Propanol.

Questions?

- 516-354-8888